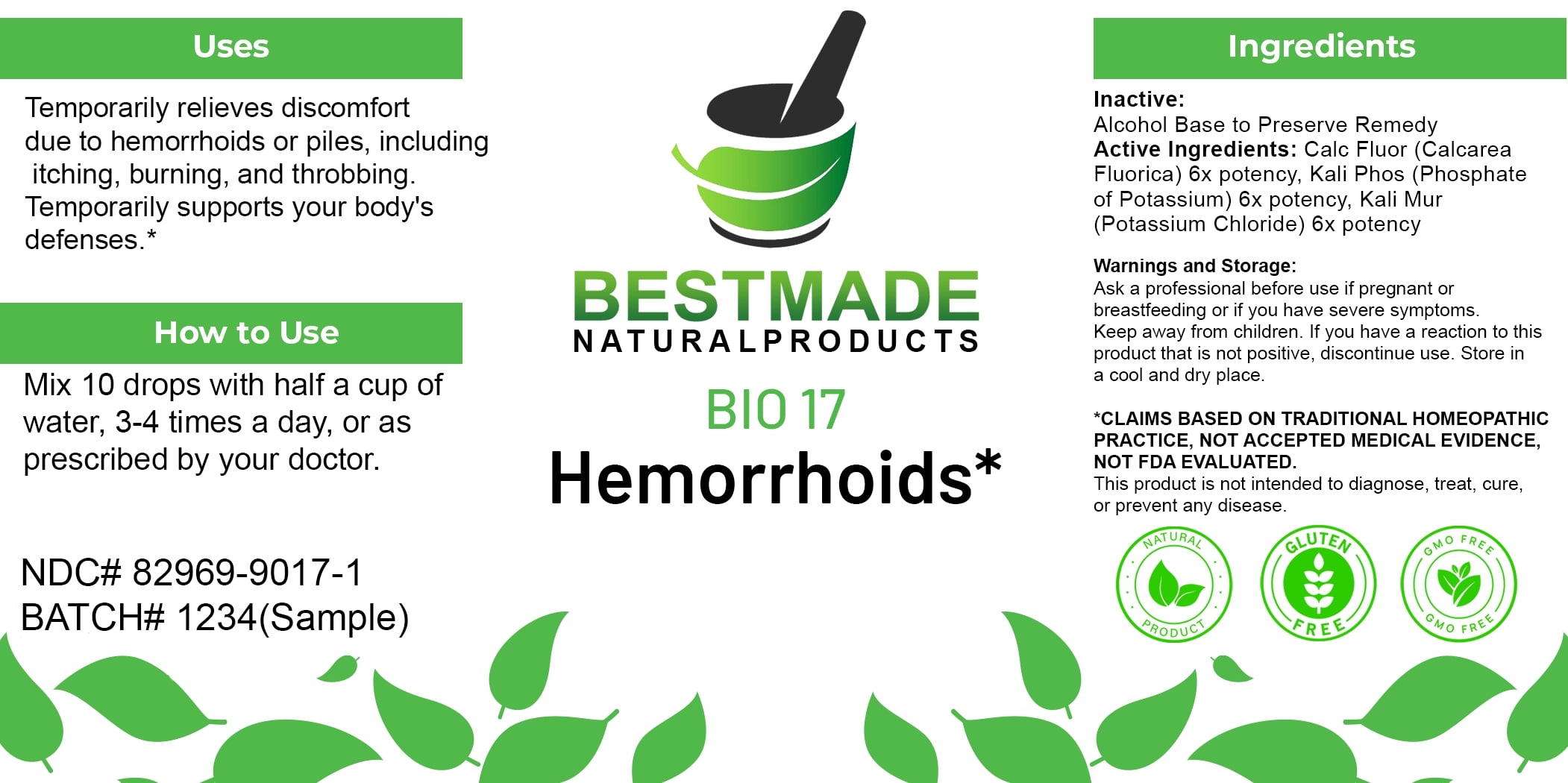 DRUG LABEL: Bestmade Natural Products BIO17
NDC: 82969-9017 | Form: LIQUID
Manufacturer: Bestmade Natural Products
Category: homeopathic | Type: HUMAN OTC DRUG LABEL
Date: 20250323

ACTIVE INGREDIENTS: POTASSIUM CHLORIDE 6 [hp_X]/6 [hp_X]; POTASSIUM PHOSPHATE, DIBASIC 6 [hp_X]/6 [hp_X]; CALCIUM FLUORIDE 6 [hp_X]/6 [hp_X]
INACTIVE INGREDIENTS: ALCOHOL 6 [hp_X]/6 [hp_X]

BIO 17 Hemorrhoids*

DOSAGE AND ADMINISTRATION

How to Use

Mix 10 drops with half a cup of water, 3-4 times a day, or as prescribed by your doctor.

ACTIVE INGREDIENT

Active Ingredients: Calc Fluor (Calcarea Fluorica) 6x potency, Kali Phos (Phosphate of Potassium) 6x potency, Kali Mur (Potassium Chloride) 6x potency

INACTIVE INGREDIENT

Ingredients

Inactive: Alcohol Base to Preserve Remedy

Uses

Temporarily relieves discomfort due to hemorrhoids or piles, including itching, burning, and throbbing. Temporarily supports your body's defenses.*

*CLAIMS BASED ON TRADITIONAL HOMEOPATHIC PRACTICE, NOT ACCEPTED MEDICAL EVIDENCE, NOT FDA EVALUATED.

This product is not intended to diagnose, treat, cure, or prevent any disease.

Uses

Temporarily relieves discomfort due to hemorrhoids or piles, including itching, burning, and throbbing. Temporarily supports your body's defenses.*

*CLAIMS BASED ON TRADITIONAL HOMEOPATHIC PRACTICE, NOT ACCEPTED MEDICAL EVIDENCE, NOT FDA EVALUATED.

This product is not intended to diagnose, treat, cure, or prevent any disease.

KEEP OUT OF REACH OF CHILDREN

Warnings and Storage:

Ask a professional before use if pregnant or breastfeeding or if you have severe symptoms. Keep away from children. If you have a reaction to this product that is not positive, discontinue use. Store in a cool and dry place.

Warnings and Storage:

Ask a professional before use if pregnant or breastfeeding or if you have severe symptoms. Keep away from children. If you have a reaction to this product that is not positive, discontinue use. Store in a cool and dry place.

*CLAIMS BASED ON TRADITIONAL HOMEOPATHIC PRACTICE, NOT ACCEPTED MEDICAL EVIDENCE, NOT FDA EVALUATED.

This product is not intended to diagnose, treat, cure, or prevent any disease.

Entire package label